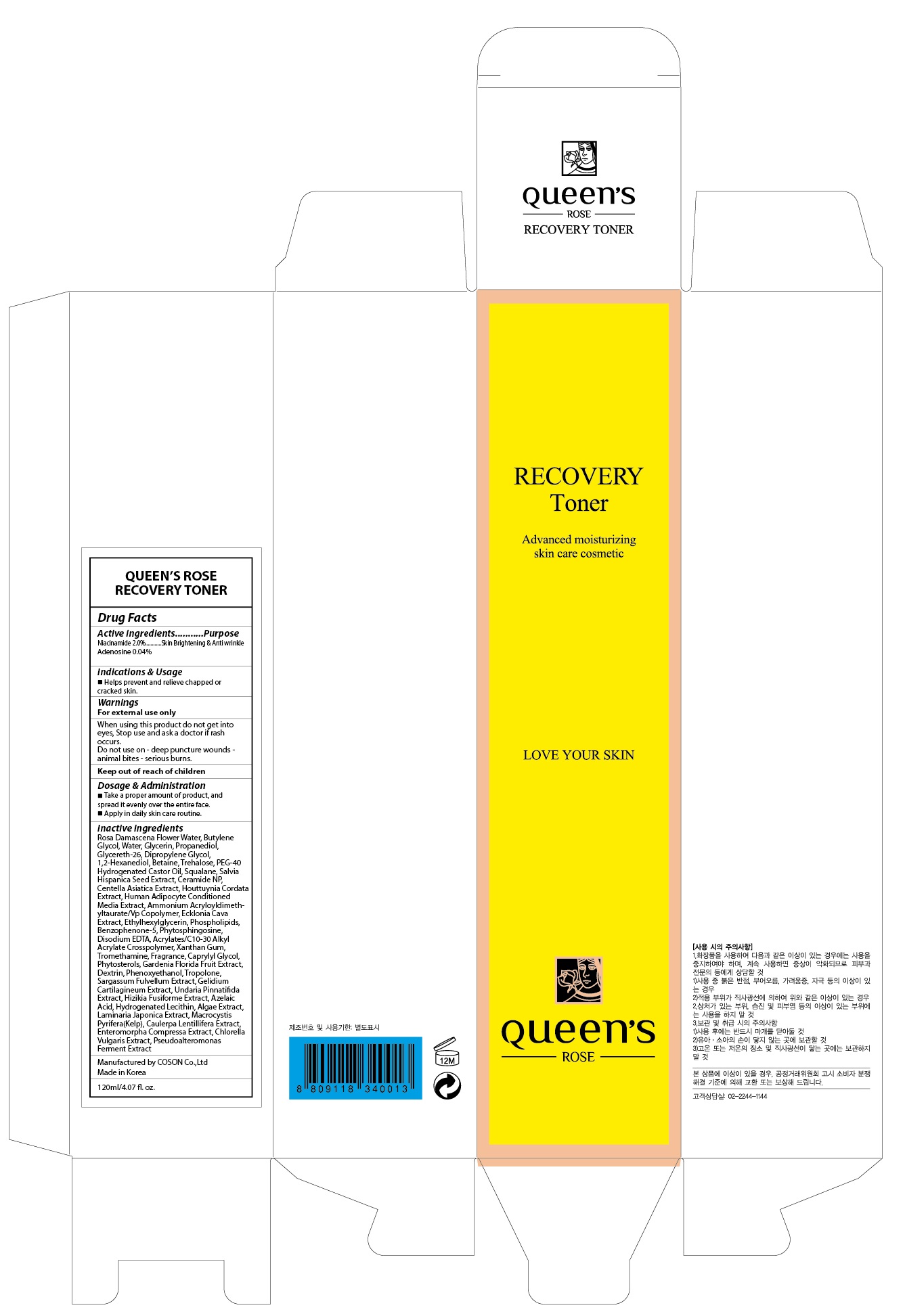 DRUG LABEL: QUEENS ROSE RECOVERY TONER
NDC: 71252-010 | Form: LIQUID
Manufacturer: Cdpharmtec Co.,ltd
Category: otc | Type: HUMAN OTC DRUG LABEL
Date: 20170324

ACTIVE INGREDIENTS: Niacinamide 2.4 g/120 mL; Adenosine 0.048 g/120 mL
INACTIVE INGREDIENTS: ROSA DAMASCENA FLOWER OIL; Water

ACTIVE INGREDIENT

Active ingredients: Niacinamide 2.0%, Adenosine 0.04%

INACTIVE INGREDIENT

Inactive ingredients: Rosa Damascena Flower Water, Butylene Glycol, Water, Glycerin, Propanediol, Glycereth-26, Dipropylene Glycol, 1,2-Hexanediol, Betaine, Trehalose, PEG-40 Hydrogenated Castor Oil, Squalane, Salvia Hispanica Seed Extract, Ceramide NP, Centella Asiatica Extract, Houttuynia Cordata Extract, Human Adipocyte Conditioned Media Extract, Ammonium Acryloyldimethyltaurate/Vp Copolymer, Ecklonia Cava Extract, Ethylhexylglycerin, Phospholipids, Benzophenone-5, Phytosphingosine, Disodium EDTA, Acrylates/C10-30 Alkyl Acrylate Crosspolymer, Xanthan Gum, Tromethamine, Fragrance, Caprylyl Glycol, Phytosterols, Gardenia Florida Fruit Extract, Dextrin, Phenoxyethanol, Tropolone, Sargassum Fulvellum Extract, Gelidium Cartilagineum Extract, Undaria Pinnatifida Extract, Hizikia Fusiforme Extract, Azelaic Acid, Hydrogenated Lecithin, Algae Extract, Laminaria Japonica Extract, Macrocystis Pyrifera(Kelp), Caulerpa Lentillifera Extract, Enteromorpha Compressa Extract, Chlorella Vulgaris Extract, Pseudoalteromonas Ferment Extract

PURPOSE

Purpose: Skin Brightening & Anti wrinkle

WARNINGS

Warnings: For external use only When using this product do not get into eyes, Stop use and ask a doctor if rash occurs. Do not use on - deep puncture wounds - animal bites - serious burns.

KEEP OUT OF REACH OF CHILDREN

INDICATIONS & USAGE

Indications & Usage: Helps prevent and relieve chapped or cracked skin.

DOSAGE & ADMINISTRATION

Dosage & Administration: - Take a proper amount of product, and spread it evenly over the entire face. - Apply in daily skin care routine.